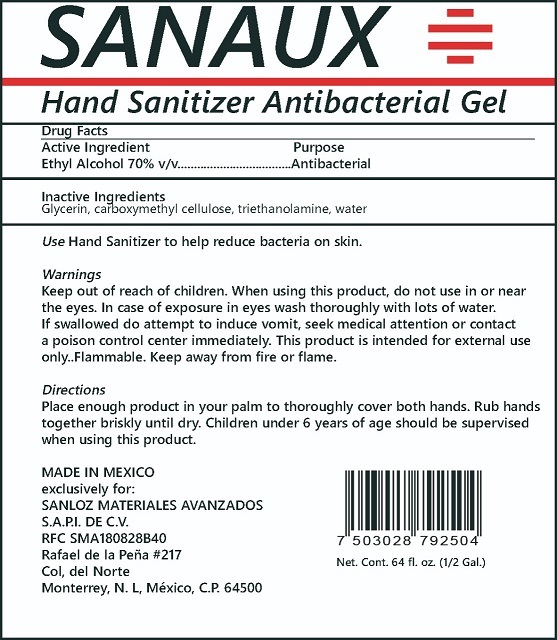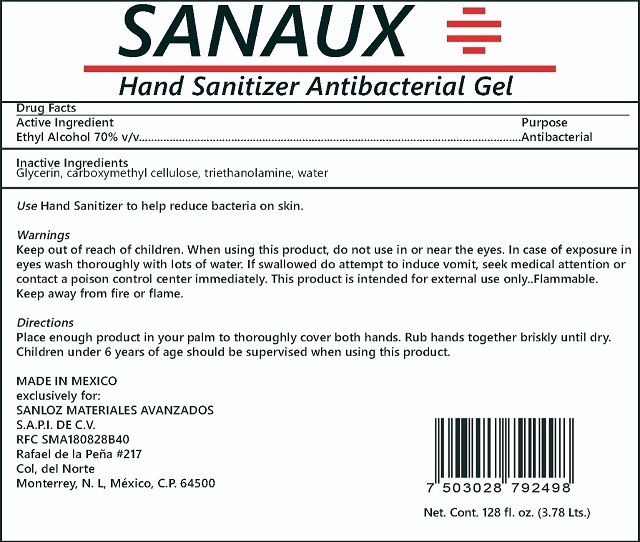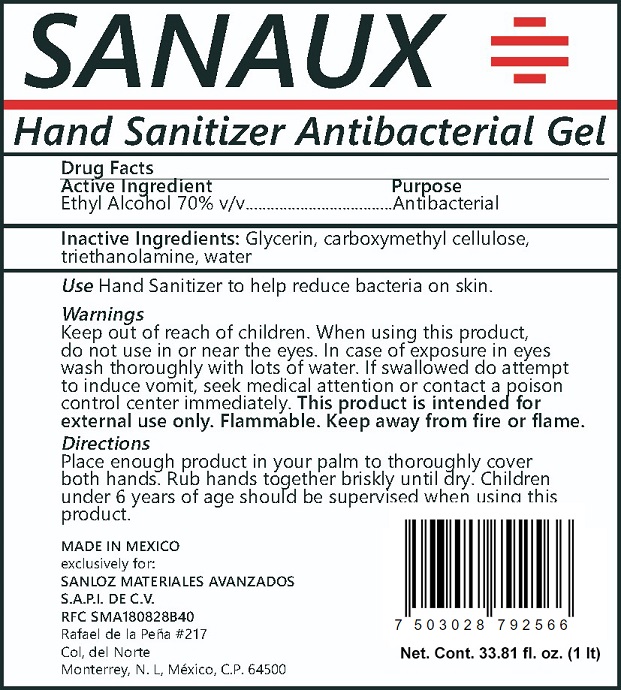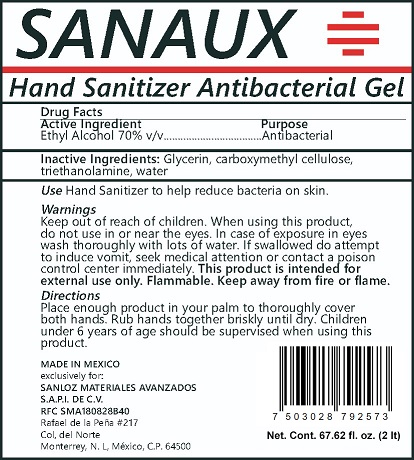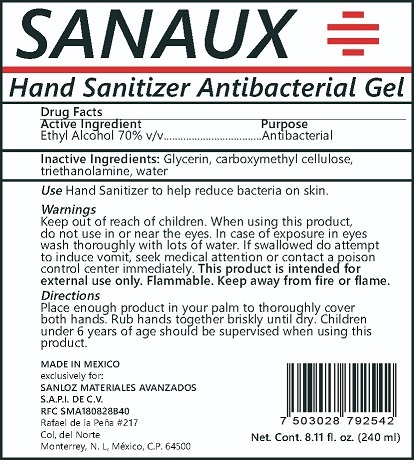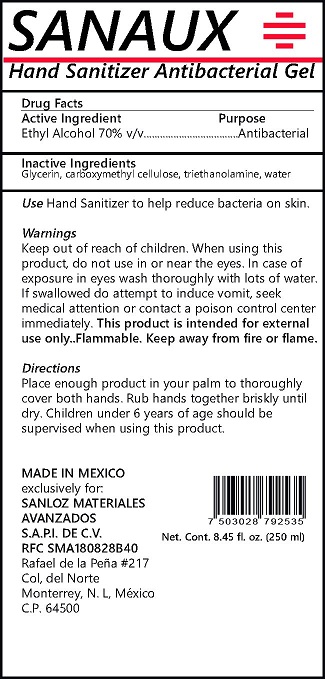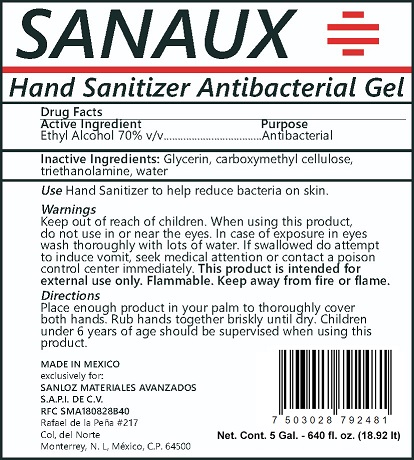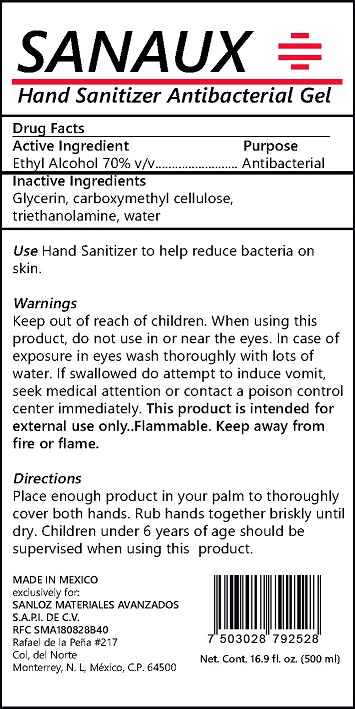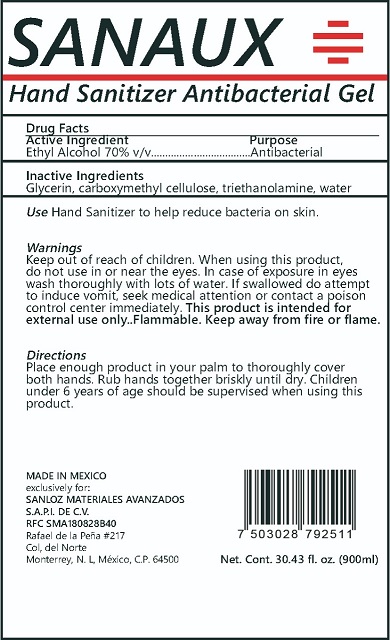 DRUG LABEL: Sanaux Hand Sanitizer Antibacterial Gel
NDC: 75509-001 | Form: GEL
Manufacturer: SANLOZ GROUP INC.
Category: otc | Type: HUMAN OTC DRUG LABEL
Date: 20200415

ACTIVE INGREDIENTS: ALCOHOL 70 mL/100 mL
INACTIVE INGREDIENTS: GLYCERIN; TROLAMINE; WATER; CARBOXYMETHYLCELLULOSE

Active Ingredient

Ethyl Alcohol 70% v/v.

Purpose

Antibacterial

Uses

Hand sanitizer to help reduce bacteria on skin.

Warnings

Keep out of reach of children.

When using this product, do not use in or near the eyes. In case of exposure in eyes wash thoroughly with lots of water.

If swallowed do not attempt to induce vomit, seek medical attention or contact poison control center immediately.

This product is intended for external use only. Flammable. Keep away from fire or flame.

Directions

Place enough product in your palm to thoroughly cover both hands. Rub hand together briskly until dry. Children under 6 years of age should be supervised when using this product.

Inactive ingredients

Glycerin, Carboxymethylcellulose, Triethanolamine, Water